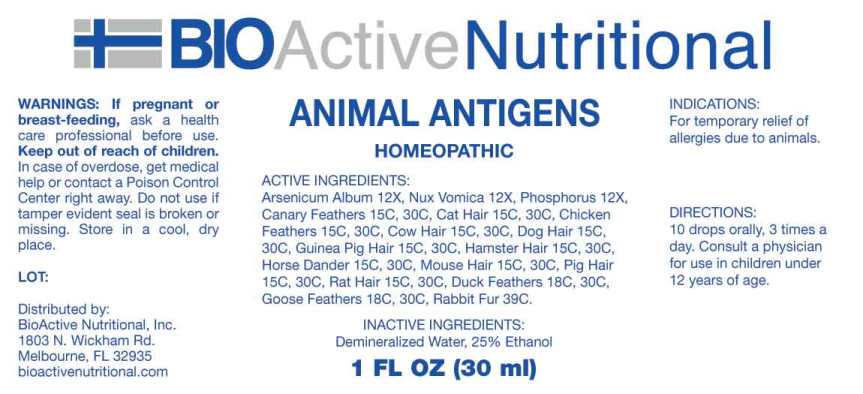 DRUG LABEL: Animal Antigens
NDC: 43857-0563 | Form: LIQUID
Manufacturer: BioActive Nutritional
Category: homeopathic | Type: HUMAN OTC DRUG LABEL
Date: 20230606

ACTIVE INGREDIENTS: ARSENIC TRIOXIDE 12 [hp_X]/1 mL; STRYCHNOS NUX-VOMICA SEED 12 [hp_X]/1 mL; PHOSPHORUS 12 [hp_X]/1 mL; SERINUS CANARIA FEATHER 15 [hp_C]/1 mL; FELIS CATUS HAIR 15 [hp_C]/1 mL; GALLUS GALLUS FEATHER 15 [hp_C]/1 mL; BOS TAURUS HAIR 15 [hp_C]/1 mL; CANIS LUPUS FAMILIARIS HAIR 15 [hp_C]/1 mL; CAVIA PORCELLUS HAIR 15 [hp_C]/1 mL; MESOCRICETUS AURATUS SKIN 15 [hp_C]/1 mL; EQUUS CABALLUS DANDER 15 [hp_C]/1 mL; MUS MUSCULUS HAIR 15 [hp_C]/1 mL; SUS SCROFA HAIR 15 [hp_C]/1 mL; RATTUS NORVEGICUS HAIR 15 [hp_C]/1 mL; ANAS PLATYRHYNCHOS FEATHER 18 [hp_C]/1 mL; ANSER ANSER FEATHER 18 [hp_C]/1 mL; ORYCTOLAGUS CUNICULUS HAIR 39 [hp_C]/1 mL
INACTIVE INGREDIENTS: WATER; ALCOHOL

Drug Facts:

ACTIVE INGREDIENTS:

Arsenicum Album 12X, Nux Vomica 12X, Phosphorus 12X, Canary Feathers 15C, 30C, Cat Hair 15C, 30C, Chicken Feathers 15C, 30C, Cow Hair 15C, 30C, Dog Hair Mix 15C, 30C, Guinea Pig Hair 15C, 30C, Hamster Hair 15C, 30C, Horse Dander 15C, 30C, Mus Musculus 15C, 30C, Pig Hair 15C, 30C, Rat Hair 15C, 30C, Duck Feathers 18C, 30C, Goose Feathers 18C, 30C, Rabbit Fur 39C.

INDICATIONS:

For temporary relief to allergies due to animals.

WARNINGS:

If pregnant or breast-feeding, ask a health care professional before use.

Keep out of reach of children. In case of overdose, get medical help or contact a Poison Control Center right away.

Do not use if tamper evident seal is broken or missing.

Store in a cool, dry place.

Keep out of reach of children. In case of overdose, get medical help or contact a Poison Control Center right away.

DIRECTIONS:

10 drops orally, 3 times a day. Consult a physician for use in children under 12 years of age.

INDICATIONS:

For temporary relief to allergies due to animals.

INACTIVE INGREDIENTS:

Demineralized Water, 25% Ethanol

QUESTIONS:

Distributed by:
BioActive Nutritional, Inc.
1803 N. Wickham Rd.
Melbourne, FL 32935
bioactivenutritional.com

PACKAGE DISPLAY LABEL:

BioActive Homeopathic

ANIMAL ANTIGENS

HOMEOPATHIC

1 FL OZ (30 ml)